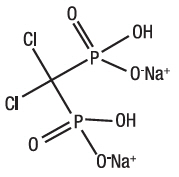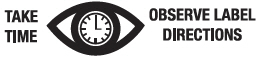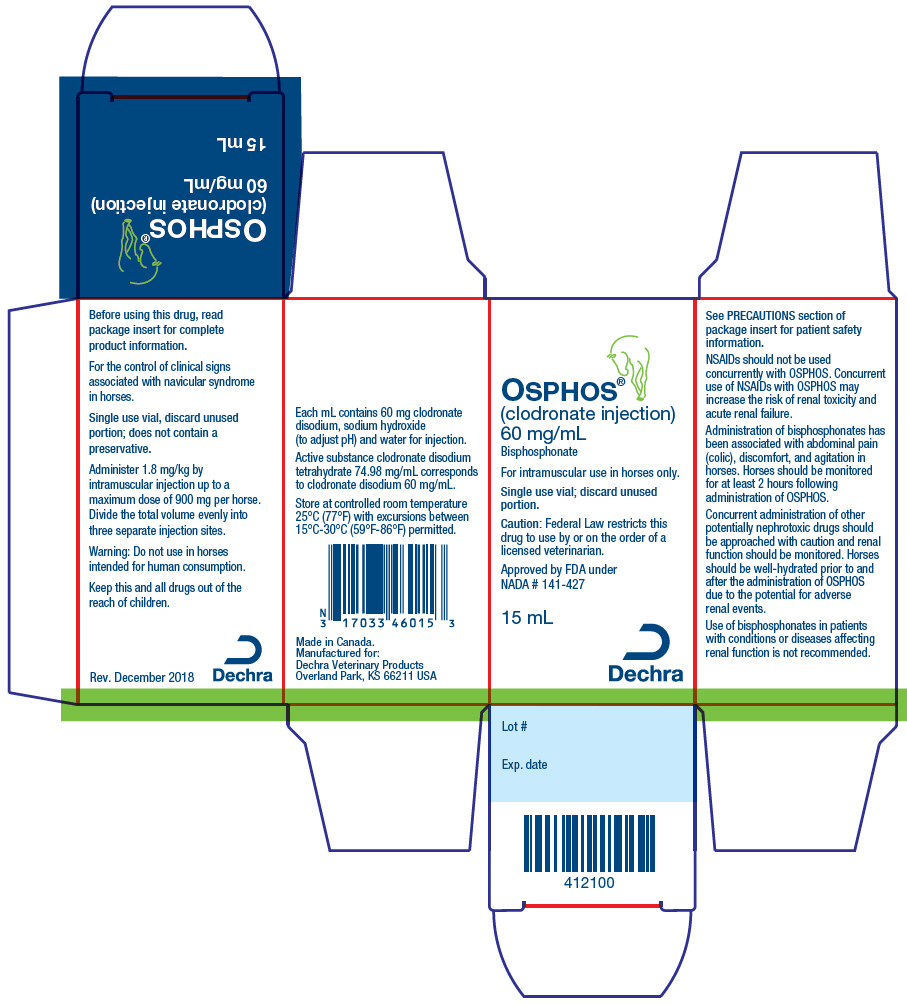 DRUG LABEL: OSPHOS
NDC: 17033-460 | Form: INJECTION, SOLUTION
Manufacturer: Dechra Veterinary Products
Category: animal | Type: PRESCRIPTION ANIMAL DRUG LABEL
Date: 20200729

ACTIVE INGREDIENTS: CLODRONATE DISODIUM 60 mg/1 mL
INACTIVE INGREDIENTS: Sodium Hydroxide; Water

OSPHOS®
(clodronate injection)

Bisphosphonate

CAUTION: Federal law (USA) restricts this drug to use by or on the order of a licensed veterinarian. For intramuscular use in horses only.

DESCRIPTION

DESCRIPTION: Clodronate disodium is a non-amino, chloro-containing bisphosphonate. Chemically, clodronate disodium is (dichloromethylene) diphosphonic acid disodium salt and is manufactured from the tetrahydrate form.

The structural formula of clodronate disodium is:

Molecular Formula: CH2Cl2Na2O6P2 Molecular Weight: 288.85

Active substance clodronate disodium tetrahydrate 74.98 mg/mL corresponds to clodronate disodium 60.0 mg/mL. Each mL contains 60 mg clodronate disodium, sodium hydroxide (to adjust pH) and water for injection.

VETERINARY INDICATIONS

INDICATION: For the control of clinical signs associated with navicular syndrome in horses.

DOSAGE AND ADMINISTRATION: Administer 1.8 mg/kg by intramuscular injection up to a maximum dose of 900 mg per horse. Divide the total volume evenly into three separate injection sites. Discard unused vial contents. OSPHOS is provided in a single use vial and does not contain a preservative.

Clinical improvement is most evident at 2 months post-treatment (see EFFECTIVENESS). Of the horses that responded to treatment with OSPHOS in the field study, 65% maintained their level of improvement through the 6 month evaluation.

If there is no response to initial therapy, the horse should be re-evaluated. For horses that initially respond to OSPHOS but do not maintain their clinical improvement for 6 months, OSPHOS may be re-administered at 3 to 6 month intervals based on recurrence of clinical signs. For horses that respond to OSPHOS and maintain clinical improvement for 6 months, OSPHOS should be re-administered after clinical signs recur.

CONTRAINDICATIONS

CONTRAINDICATIONS: Horses with hypersensitivity to clodronate disodium should not receive OSPHOS.

Do not use in horses with impaired renal function or with a history of renal disease.

WARNINGS

WARNINGS: Do not use in horses intended for human consumption.

NSAIDs should not be used concurrently with OSPHOS. Concurrent use of NSAIDs with OSPHOS may increase the risk of renal toxicity and acute renal failure.

Human Warnings: Not for human use. Keep this and all drugs out of the reach of children. Consult a physician in case of accidental human exposure.

PRECAUTIONS

PRECAUTIONS: OSPHOS has been associated with renal toxicity. Concurrent administration of other potentially nephrotoxic drugs should be approached with caution and renal function should be monitored. Use of bisphosphonates in patients with conditions or diseases affecting renal function is not recommended.

Horses should be well-hydrated prior to and after the administration of OSPHOS due to the potential for adverse renal events. Water intake and urine output should be monitored for 3-5 days post-treatment and any changes from baseline should elicit further evaluation.

As a class, bisphosphonates may be associated with gastrointestinal and renal toxicity. Sensitivity to drug associated adverse reactions varies with the individual patient. Renal and gastrointestinal adverse reactions may be associated with plasma concentrations of the drug. Bisphosphonates are excreted by the kidney; therefore, conditions causing renal impairment may increase plasma bisphosphonate concentrations resulting in an increased risk for adverse reactions.

Administration of bisphosphonates has been associated with abdominal pain (colic), discomfort, and agitation in horses. Clinical signs usually occur shortly after drug administration and may be associated with alterations in intestinal motility. In horses treated with OSPHOS these clinical signs usually began within 2 hours of treatment. Horses should be monitored for at least 2 hours following administration of OSPHOS.

Bisphosphonates affect plasma concentrations of some minerals and electrolytes such as calcium, magnesium and potassium, immediately post-treatment, with effects lasting up to several hours. Caution should be used when administering bisphosphonates to horses with conditions affecting mineral or electrolyte homeostasis (e.g. hyperkalemic periodic paralysis, hypocalcemia, etc.).

The safe use of OSPHOS has not been evaluated in horses less than 4 years of age. The effect of bisphosphonates on the skeleton of growing horses has not been studied; however, bisphosphonates inhibit osteoclast activity which impacts bone turnover and may affect bone growth.

Bisphosphonates should not be used in pregnant or lactating mares, or mares intended for breeding. The safe use of OSPHOS has not been evaluated in breeding horses or pregnant or lactating mares. Bisphosphonates are incorporated into the bone matrix, from where they are gradually released over periods of months to years. The extent of bisphosphonate incorporation into adult bone, and hence, the amount available for release back into the systemic circulation, is directly related to the total dose and duration of bisphosphonate use. Bisphosphonates have been shown to cause fetal developmental abnormalities in laboratory animals. The uptake of bisphosphonates into fetal bone may be greater than into maternal bone creating a possible risk for skeletal or other abnormalities in the fetus. Many drugs, including bisphosphonates, may be excreted in milk and may be absorbed by nursing animals.

Increased bone fragility has been observed in animals treated with bisphosphonates at high doses or for long periods of time. Bisphosphonates inhibit bone resorption and decrease bone turnover which may lead to an inability to repair microdamage within the bone. In humans, atypical femur fractures have been reported in patients on long term bisphosphonate therapy; however, a causal relationship has not been established.

ADVERSE REACTIONS

ADVERSE REACTIONS: One hundred forty-six horses (111 OSPHOS, 35 saline control) of various breeds, 4 to 22 years of age, and weighing 807 to 1,322 pounds were included in the field study safety analysis.

Following treatment on Day 0, 10 horses had clinical signs of discomfort or nervousness, cramping, pawing, and/or colic within 2 hours post-treatment. One horse experiencing colic and hives required treatment with supportive care to resolve clinical signs. In 8 of the 10 horses, 10 to 15 minutes of hand walking resulted in resolution of clinical signs. In one horse, clinical signs resolved without hand walking. Three additional horses experienced lip licking, yawning, and/or head shaking. Adverse reactions occurring within 2 hours post-treatment with OSPHOS or the saline control are summarized in Table 1.

Table 1: Adverse Reactions Occurring within 2 Hours Post-treatment
Clinical Sign | OSPHOS (n=111) | Control (n=35)
Uncomfortable, Nervous, Colic, and/or Pawing | 9.0% (10) | 0% (0)
Lip licking | 5.4% (6) | 0% (0)
Yawning | 4.5% (5) | 0% (0)
Head shaking | 2.7% (3) | 0% (0)
Injection site swelling | 1.8% (2) | 2.9% (1)
Colic requiring treatment [This horse experienced colic and hives and recovered with supportive treatment.] | 0.9% (1) | 0% (0)
Hives/Pruritus | 0.9% (1) | 0% (0)

POST-APPROVAL EXPERIENCE (December 2018): The following adverse events are based on post-approval adverse drug experience reporting. Not all adverse events are reported to FDA/CVM. It is not always possible to reliably estimate the adverse event frequency or establish a causal relationship to product exposure using these data.

The following adverse events are listed in decreasing order of reporting frequency: renal failure, polyuria, polydipsia, abdominal pain, anorexia, lethargy, hypercalcemia, behavioral disorder (e.g.: head shaking, flehmen response, lip licking), discomfort, hyperkalemia, hyperactivity, recumbency, hyperthermia, injection site reactions (pain, edema, inflammation), muscle tremor, urticaria, hyperglycemia, and fracture.

In some cases, death has been reported as an outcome of the adverse events listed above (See PRECAUTIONS).

Contact Information: For a copy of the SDS or to report suspected adverse drug events, contact Dechra at (866) 933-2472. For additional information about adverse drug experience reporting for animal drugs, contact FDA at 1-888-FDA-VETS or online at http://www.fda.gov/AnimalVeterinary/SafetyHealth.

INFORMATION FOR OWNERS/CAREGIVERS

INFORMATION FOR HORSE OWNERS: Owners should be advised to:

- NOT administer NSAIDs.
- Ensure horses have access to adequate water before and after administration of OSPHOS.
- Observe their horse for at least 2 hours post-treatment for signs of colic, agitation, and/or abnormal behavior.
- If a horse appears uncomfortable, nervous, or experiences cramping post-treatment, hand walk the horse for 15 minutes. If signs do not resolve contact the veterinarian.
- Monitor water intake and urine output for 3-5 days post-treatment.
- Contact their veterinarian if the horse displays abnormal clinical signs such as changes in drinking and urination, appetite, and attitude.

(See PRECAUTIONS and Post-Approval Experience sections.)

CLINICAL PHARMACOLOGY

CLINICAL PHARMACOLOGY: Clodronate disodium is a non-nitrogen containing bisphosphonate that inhibits bone resorption by binding to calcium phosphate crystals (inhibiting their formation and dissolution), and by exerting direct cellular effects on osteoclasts (inhibiting osteoclast cell function)^1. Bound to bone matrix, clodronate disodium enters resorbing osteoclasts, alters their morphology and reduces the number of active osteoclasts, regardless of the cause of osteoclast activity^2,3.

In humans, 60 to 80% of clodronate disodium administered intravenously is eliminated unchanged in the urine and 5% in the feces^2; the remainder of the administered dose is distributed to bone. The bone residence time in horses could not be estimated. However, in numerous studies, the half-life of clodronate disodium in rodent bone (long bones and lumbar vertebrae) has been estimated to be months to years.

After intramuscular injection, clodronate disodium is rapidly absorbed and cleared from the plasma. Within a dosing range of 1.8 to 5.4 mg/kg (n=8 per dose group), the Cmax values increased in proportion to the dose. However, dose related changes were observed after the third administration of a regimen consisting of a single 5.4 mg/kg intramuscular injection administered once every 28 days. In this 3× dose group, a decrease in apparent total systemic clearance (CL/F) was seen (0.08 mL/hr + 0.02; mean + standard deviation), resulting in a greater than proportional increase in systemic drug exposure (AUC, 62.49 hr*mcg/mL ± 18.52) and plasma elimination T ½ (2.89 hours ± 1.33). In comparison, the estimated mean CL/F in horses receiving the 1× (1.8 mg/kg) dose was 0.12 mL/hr + 0.02 (mean + standard deviation) and the corresponding mean pharmacokinetic parameters were 5.36 ± 0.98 mcg/mL (Cmax), 12.15 ± 1.83 hr*mcg/mL (AUC), 1.65 ± 0.52 hours (T ½) and 20 minutes (Tmax).

EFFECTIVENESS: A double masked 3:1 randomized, negative control, multi-site field study evaluated the effectiveness of a single dose of 1.4 mg/kg OSPHOS (maximum dose of 900 mg/horse) for the control of clinical signs associated with navicular syndrome in horses. Enrolled horses had a unilateral or bilateral forelimb lameness of Grade ≥ 2 on the AAEP lameness scale (Grade 0 to 5) and a diagnosis of navicular syndrome based on lameness exam, diagnostic nerve blocks, and radiographic signs indicative of the bony changes associated with navicular syndrome. Horses with radiographic signs indicating concurrent soft tissue injury, osteoarthritis, fractures, or any condition other than the bony changes related to navicular syndrome were not eligible for enrollment. A horse was considered a treatment success if the lameness grade in the primarily affected limb improved by at least 1 AAEP grade and there was no worsening of lameness grade in the other forelimb on Day 56 post-treatment as compared to the pre-treatment assessment. Lameness scores were also recorded on Day 28 and Day 180.

Of the 211 horses screened for enrollment, 146 horses received treatment (111 OSPHOS and 35 saline control). 29% of horses screened for enrollment were not eligible based on radiographic findings. 114 horses (86 OSPHOS, 28 saline control) were included in the statistical analysis. Effectiveness was evaluated on Day 56 post-treatment. On Day 56, 68 of the 86 OSPHOS treated horses and 1 out of 28 saline treated horses were treatment successes. Based on the statistical analysis, the estimated least squares mean success rates are 74.7% and 3.3% for the OSPHOS and saline treated groups, respectively. The difference in success rates is significant at P=0.0028.

Table 2: Day 56 Treatment Success Rate
Study Day | OSPHOS | Saline | P Value [P value and estimated success rates are based on back-transformed mean estimates from the statistical analysis.]
56 | 74.7% | 3.3% | 0.0028

Treatment success based on Day 28 and Day 180 lameness scores was also assessed but not statistically analyzed. At Day 28, 67.4% (60/89) OSPHOS treated horses were considered successes, compared to 20.7% (6/29) in the saline treated group. Day 56 treatment successes were followed to the Day 180 assessment, and Day 56 treatment failures were also considered failures at Day 180. Of the 68 OSPHOS treated horses that were deemed treatment successes on Day 56, 60 were evaluable at Day 180. Of these 60 horses, 51 remained treatment successes at Day 180 based on improvement in lameness grade as compared to Day 0. However, 21 of these 60 evaluable horses demonstrated an increase in lameness grade at Day 180 as compared to their Day 56 evaluation. Including the 18 treatment failures at Day 56, the estimated overall success rate for OSPHOS at Day 180 is 65.4% (51/78).

Table 3: Day 28 and Day 180 Treatment Success Rates
Study Day | OSPHOS | Saline
28 | 67.4% (60/89) | 20.7% (6/29)
180 | 65.4% (51/78) [The 18 horses that were treatment failures on Day 56 were considered to remain treatment failures at Day 180. No Day 180 lameness evaluation was performed on these horses. 60 horses (all OSPHOS treated horses) completed the Day 180 lameness evaluation.] | None evaluable

ANIMAL SAFETY: Two studies were conducted to assess the safety of OSPHOS in horses, a six month target animal safety (TAS) study and a two phase study evaluating the safety of concurrent use of the recommended dose of OSPHOS with an NSAID and a single 5× (9 mg/kg) dose of OSPHOS.

Target Animal Safety Study: In the TAS study, OSPHOS was administered to 32 healthy adult horses at 0, 1.8, 3.6 and 5.4 mg/kg (0, 1, 2, and 3× the recommended dose) every 28 days for 6 consecutive months. OSPHOS was administered by intramuscular injection with the total volume divided evenly into at least three separate injection sites with a maximum of 15 mL per injection site.

In the TAS study, the most common post-treatment observations were clinical signs related to abdominal discomfort (colic) and the central nervous system. The incidence of colic was dose related. In the TAS study, colic was observed following 94% (45/48) of 3× treatment administrations, 54% (26/48) of 2× treatment administrations, 4% (2/48) of 1× treatment administrations, and 8% (4/48) of 0× treatment administrations. 80% (36/45) of the 3× horses, 31% (8/26) of 2× horses and none of the 1× (0/2) and 0× (0/4) horses required hand walking to relieve clinical signs associated with colic. In the 3× group, clinical signs of colic often persisted after hand walking and horses were often walked more than once. Colic related clinical signs began shortly after administration (ranging from 1 to 227 minutes post-treatment). No horses in any treatment group received medical treatment and all horses returned to normal within 5.5 hours post-treatment.

In the TAS study, post-treatment clinical signs also included yawning, flehmen, tongue rolling, head shaking and neck writhing. The signs were observed in 50% (4/8) of 0×, 100% (8/8) of 1×, 88% (7/8) of 2×, and 100% (8/8) of 3× horses. All horses returned to normal within 5.5 hours post-treatment.

Table 4: Incidence of Abnormal Clinical Signs in the TAS Study
 | Number of Observations per Treatment Group (N=48 treatment administrations per group)
Clinical Sign | 0× | 1× | 2× | 3×
Colic [Signs of colic included repeated lying down and rising, rolling, kicking at the abdomen, stretching of the abdomen and/or other typical signs of abdominal discomfort.] | 4 | 2 | 26 | 45
Colic requiring hand walking | 0 | 0 | 8 | 36
Yawning | 5 | 17 | 16 | 30
Flehmen | 0 | 0 | 8 | 2
Tongue rolling | 1 | 10 | 8 | 10
Head shaking | 1 | 5 | 3 | 7
Neck writhing | 0 | 0 | 0 | 6
Pawing | 4 | 4 | 12 | 23
Agitation | 1 | 1 | 7 | 10
Depression | 0 | 2 | 5 | 21
Muscle fasciculations/Trembling | 0 | 0 | 1 | 4

Injection site reactions were identified in three 0×, four 1×, two 2×, and one 3× horse. One 1× horse had injection site reactions on two separate treatment days. Injection site reactions in OSPHOS treated horses were characterized by soft or firm swellings, ranged in size from 0.5 cm diameter to 7 × 28 cm, and resolved within 10 days. Clinical pathology evaluations showed a dose related trend for increases in BUN and creatinine post-treatment with the 2× and 3× dose groups having statistically significant elevations as compared to the 0× dose group. Horses in all OSPHOS treated groups had dose dependent elevations in BUN concentrations above the reference range (up to 41 mg/dL; reference range 8-25 mg/dL). Three 3× horses had creatinine concentrations above the reference range (up to 2.5 mg/dL; reference range 0.9-1.9 mg/dL) for up to 12 hours post-treatment. A dose related trend for an increase in potassium was observed for up to 6 hours post-treatment. Individual animal potassium concentrations were within the reference range with the exception of two 3× horses with post-treatment potassium concentrations up to 5.3 mg/dL (reference range 3-5 mg/dL). Decreases in chloride and increases in glucose, creatine kinase, and aspartate aminotransferase were also observed post-treatment. End of study evaluations concluded that bone density (bone mineral concentration) and bone strength (mechanical testing of cortical bone) remained similar between all dose groups.

Two Phase Pilot Study: In Phase I of a two phase pilot study, six horses were administered phenylbutazone orally twice a day at a dose of 4.4 mg/kg on Days 0 to 3, administered OSPHOS at 1.8 mg/kg (1×) by intramuscular injection into 3 sites once on Day 4, and continued on phenylbutazone orally twice a day at a dose of 2.2 mg/kg on Days 4 to 6. In Phase II of the pilot study, after a 15 day washout, the same six horses were administered a single dose of OSPHOS at 9 mg/kg (5×) by intramuscular injection divided evenly into 5 separate injection sites. No NSAIDs were administered in Phase II.

In Phase I, three horses had post-treatment elevations in BUN above the reference range (up to 42 mg/dL; reference range 8-25 mg/dL). BUN concentrations returned to normal prior to Phase II of the study. In Phase II, five out of six horses developed changes in attitude associated with signs of agitation or nervousness including pawing, circling, and tail twitching within 6 minutes of dosing. Four of six horses also developed clinical signs including excessive yawning, flehmen, tongue rolling, head shaking, and head bobbing. All six horses developed mild to moderate muscle fasciculations between 2 and 30 minutes post-treatment. By 30 minutes post-treatment, four out of six horses also developed signs of discomfort and possible abdominal pain including full body stretching, repetitive lying down and rising, and kicking at the abdomen. At approximately one hour post-treatment, one horse exhibited agitation and clinical signs of colic requiring medical therapy. The horse responded to medical therapy and was clinically normal at 7 hours post-treatment. Three out of six horses developed temporary gait abnormalities that included mild to moderate hypermetria, spasticity, or mild ataxia. Four out of six horses developed mildly elevated BUN concentrations by 48 hours post-treatment and one horse had a creatinine concentration slightly above the reference range (2.0 mg/dL; reference range 0.9-1.9 mg/dL) for 12 hours post-treatment.

STORAGE AND HANDLING

STORAGE INFORMATION: Store at controlled room temperature 25°C (77°F) with excursions between 15°C-30°C (59°F-86°F) permitted. Single use vial; discard unused portion.

HOW SUPPLIED

HOW SUPPLIED: OSPHOS is supplied in cartons with each carton containing one clear glass 20 mL vial with 15 mL (900 mg) clodronate disodium (60 mg/mL) per vial.

NDC 17033-460-15

MANUFACTURED FOR:
Dechra Veterinary Products
7015 College Boulevard, Suite 525
Overland Park, KS 66211 USA

For a copy of the Safety Data Sheet (SDS) or to report adverse reactions call Dechra Veterinary Products at (866) 933-2472.

Manufactured in Canada.

Approved by FDA under NADA # 141-427

US Patent 7,781,420

OSPHOS is a registered trademark of Dechra Ltd. All rights reserved.

© 2018 Dechra Ltd.

REFERENCES

^1 Fleisch H. 1987. Bisphosphonates-history and experimental basis. Bone 8: S23-28.
^2 Plosker GL, Goa KL. 1994. Clodronate. A review of its pharmacological properties and therapeutic efficacy in resorptive bone disease. Drugs 47: 945-982.
^3 Flanagan AM, Chambers TJ. 1989. Dichloromethylene bisphosphonate (Cl2MBP) inhibits bone resorption through injury to osteoclasts that resorb Cl2MBP-coated bone. Bone Miner: 6:33-43.

Rev. December 2018

Dechra

PRINCIPAL DISPLAY PANEL - 15 mL Vial Carton

OSPHOS®
(clodronate injection)
60 mg/mL
Bisphosphonate

For intramuscular use in horses only.

Single use vial; discard unused
portion.

Caution: Federal Law restricts this
drug to use by or on the order of a
licensed veterinarian.

Approved by FDA under
NADA # 141-427

15 mL

Dechra